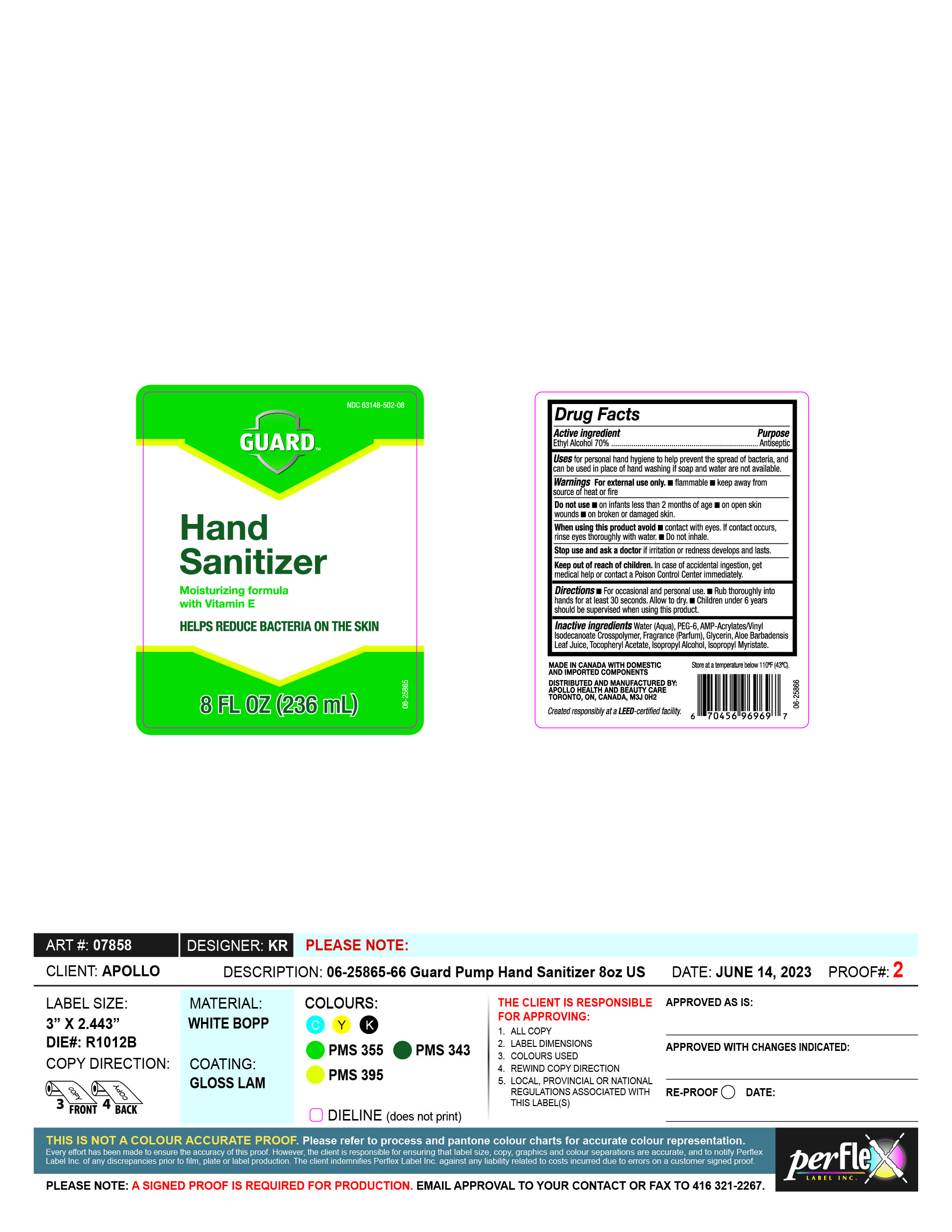 DRUG LABEL: Guard
NDC: 63148-502 | Form: GEL
Manufacturer: Apollo Health and Beauty Care
Category: otc | Type: HUMAN OTC DRUG LABEL
Date: 20250104

ACTIVE INGREDIENTS: ALCOHOL 70 mL/100 mL
INACTIVE INGREDIENTS: ACRYLATES/VINYL ISODECANOATE CROSSPOLYMER (10000 MPA.S NEUTRALIZED AT 0.5%); POLYETHYLENE GLYCOL 300; GLYCERIN; WATER; ISOPROPYL MYRISTATE; ISOPROPYL ALCOHOL; ALOE VERA LEAF; FRAGRANCE CLEAN ORC0600327; .ALPHA.-TOCOPHEROL ACETATE

NDC- 63148-502, Guard Hand Sanitizer

Active Ingredient

Ethyl Alcohol 70%

Purpose

Antiseptic

Uses

For personal hand hygine to help prevent the spread of bacteria, and can be used in place of hand washing if soap and water are not available.

Warnings

For external use only.

- Flammable
- Keep away from source of heat or fire.

Do not use

- On infants less than 2 months of age.
- On open skin wounds
- On broken or damaged skin.

When using this product avoid

- contact with eyes. If contact occurs, rinse eyes thoroughly with water.
- Do not inhale.

Stop use and ask a doctor

if irritation or redness develops and lasts.

Keep out of reach of children

In case of accidental ingestion, get medical help or contact Poison Control Center immediately.

Directions

- For occassional and Personal use.
- Rub thoroughly into hands for at least 30 seconds. Allo to dry.
- Children under 6 years should be supervised when using this product.

Inactive Ingredients

Water (Aqua), PEG-6, AMP-Acrylates/vinyl Isodecanoate Crosspolymer, Fragrance (Parfum), Glycerin, Aloe Barbadensis Leaf Juice, Tocopheryl Acetate, Isopropyl Alcohol, Isopropyl Myristate.